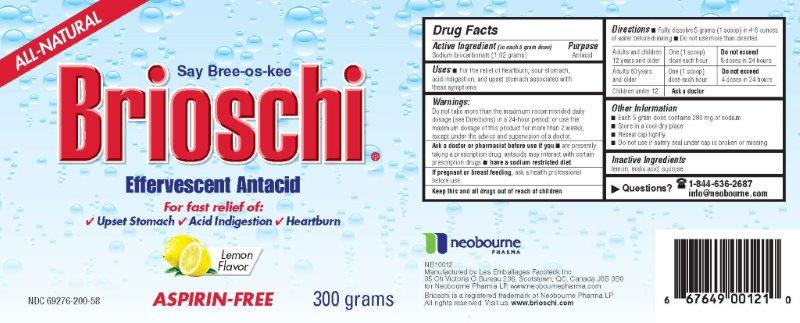 DRUG LABEL: Brioschi Effervescent Antacid
NDC: 69276-200 | Form: GRANULE, EFFERVESCENT
Manufacturer: Neobourne Pharma LP
Category: otc | Type: HUMAN OTC DRUG LABEL
Date: 20181218

ACTIVE INGREDIENTS: SODIUM BICARBONATE 1.02 g/5 g
INACTIVE INGREDIENTS: MALIC ACID; SUCROSE; LEMON

Brioschi Effervescent Antacid 300g Bottle

Drug Facts

Active Ingredient (in each 5 gram dose)

Sodium bicarbonate (1.02 grams)

Purpose

Antacid

Uses

For the relief of heartburn, sour stomach, acid indigestion, and upset stomach associated with these symptoms.

Warnings

Do not take more than the maximum recommended daily dosage (see Directions) in a 24-hour period, or use the maximum dosage of this product for more than 2 weeks, except under the advice and supervision of a doctor.

Ask a doctor or pharmacist before use if you • are presently taking a prescription drug; antacids may interact with certain prescription drugs • have a sodium restricted diet

PREGNANCY OR BREAST FEEDING

If pregnant or breast feeding, ask a health professional before use.

KEEP OUT OF REACH OF CHILDREN

Keep this and all drugs out of reach of children.

Directions

Fully dissolve 5 grams (1 scoop) in a 4-6 ounces of water before drinking • do not use more than directed

Adults and children 12 years and older | Adults 60 years and older | Children under 12
One dose (1 scoop) each hour | One dose (1 scoop) each hour | Ask a doctor
Do not exceed 8 doses in 24 hours | Do not exceed 4 doses in 24 hours

Other Information

• Each 5 gram dose contains 280 mg of sodium

• Store in a cool dry place

• Reseal cap tightly

• Do not use if safety seal under cap is broken or missing

Inactive Ingredients

lemon, malic acid, sucrose

Questions?

1-844-636-2687 or info@neobourne.com

neobourne PHARMA

Manufactured by Les Emballages Facoteck Inc.

35 Ch Victoria 0 Bureau 236, Scotstown, QC, Canada J0B 3B0

for Neobourne Pharma LP. www.neobournepharma.com

Brioschi is a registered trademark of Neobourne Pharma LP.

All rights reserved. Visit us: www.brioschi.com

Principal Display Panel - Brioschi Effervescent Antacid 300g Bottle

ALL-NATURAL

Say Bree-os-kee

Brioschi.

Effervescent Antacid

For fast relief of:

Upset Stomach

Acid Indigestion

Heartburn

Lemon Flavor

NDC 69276-200-58

ASPIRIN-FREE

300 grams